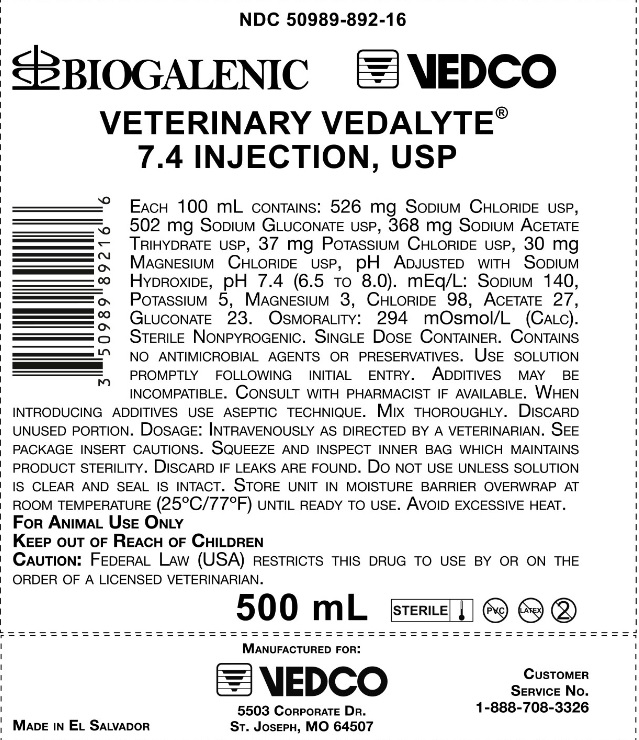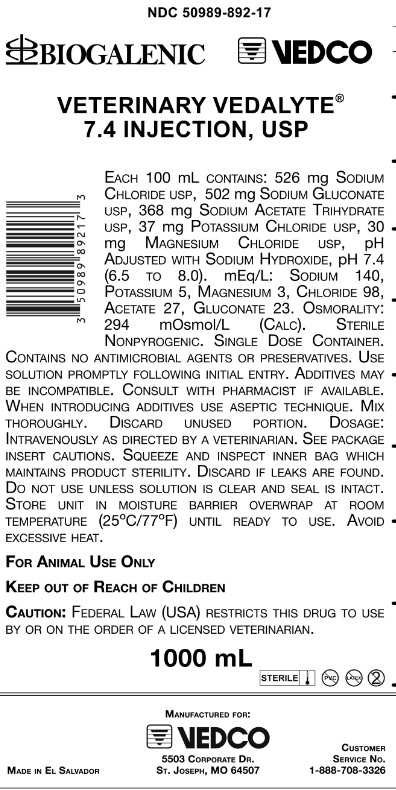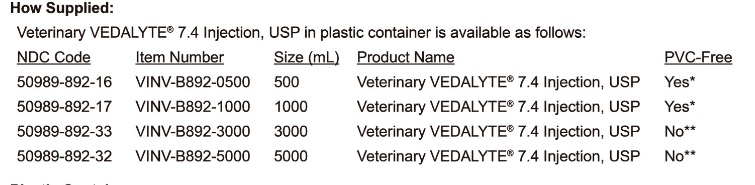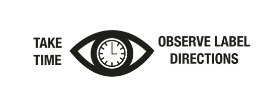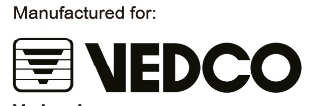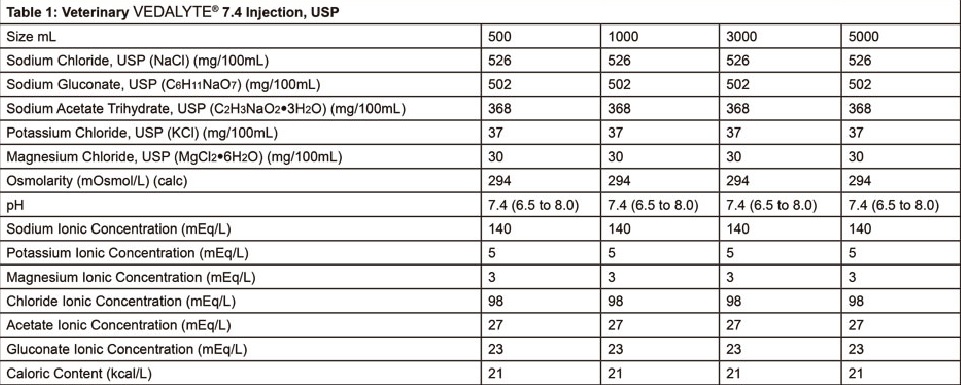 DRUG LABEL: Veterinary Vedalyte
NDC: 50989-892 | Form: INJECTION
Manufacturer: Vedco, Inc.
Category: animal | Type: PRESCRIPTION ANIMAL DRUG LABEL
Date: 20161012

ACTIVE INGREDIENTS: SODIUM CHLORIDE 526 mg/100 mL; SODIUM GLUCONATE 502 mg/100 mL; SODIUM ACETATE 368 mg/100 mL; POTASSIUM CHLORIDE 37 mg/100 mL; MAGNESIUM CHLORIDE 30 mg/100 mL

Veterinary VEDALYTE 7.4 Injection, USP

For Animal Use Only

Description

Veterinary VEDALYTE 7.4 Injection, USP is a sterile, nonpyrogenic isotonic solution for fluid and electrolyte replenishment in single dose containers for intravenous administration. It contains no antimicrobial agents or preservatives. Discard unused portion. The pH is adjusted with sodium hydroxide. Composition, osmolarity, pH, ionic concentration and caloric content are shown in Table 1:

Clinical Pharmacology

Veterinary VEDALYTE 7.4 Injection, USP administered intravenously has a value as a source of water, electrolytes and calories. Normal physiological osmolarity range is 280 to 310 mOsmol/L. Administration of substantially hypertonic solutions may cause vein damage. It is capable of inducing diuresis, depending on the clinical condition of the patient.

Veterinary VEDALYTE 7.4 Injection, USP produces a metabolic alkalinilizing effect. Acetate and gluconate ions are metabolized ultimately to carbon dioxide and water, which requires consumption of hydrogen cations

Indications and Usage

Veterinary VEDALYTE 7.4 Injection, USP is indicated as a source of water and electrolytes or as an alkalinizing agent

Veterinary VEDALYTE 7.4 Injection, USP is compatible with blood or blood components. it may be administered prior to or following the infusion of blood through the same administration set (i.e. as a primary solution), added to or infused concurrently with blood components or used a diluent in the transfusion of packed erythrocytes. VEDALYTE 7.4 Injection, USP and 0.9% Sodium Chloride Injection, USP are equally compatible with blood or blood components

Contraindications

None Known

Warnings

Veterinary VEDALYTE 7.4 Injection, USP should be used with great care, if at all, in patients with congestive heart failure, severe renal insufficiency, and in clinical states in which there exists edema with sodium retention.

Veterinary VEDALYTE 7.4 Injection, USP should be used with great care, in patients with hyperkalemia, severe renal failure, and in conditions in which potassium retention is present.

Veterinary VEDALYTE 7.4 Injection, USP should be used with great care, in patients with metabolic or respiratory alkalosis. The administration of acetate or gluconate ions should be done with great care in those conditions in which there is an increased level or an impaired utilization of these ions, such as severe hepatic insufficiency.

The intravenous administration of Veterinary VEDALYTE 7.4 Injection, USP can cause fluid and/or solute overloading resulting in dilution of serum electrolyte concentrations, overhydration, congested states, or pulmonary edema. The risk of dilutional states is inversely proportional to the electrolyte concentration of the injections. The risk of solute overload causing congested states with peripheral and pulmonary edema is directly proportional to the electrolyte concentrations of the injections.

In patients with diminished renal function, administration of lactated Ringer's Injection, USP may result in sodium or potassium retention.

Adverse Reaction

Reactions which may occur because of the solution or the technique of administration include febrile response, infection at the site of injection, venous thrombosis or phlebitis extending from the site of injection, extravasation, and hypervolemia. If an adverse reaction does occur, discontinue the infusion, evaluate the patient, institute appropriate therapeutic countermeasures and save the remainder of the fluid for examination if deemed necessary.

Precautions

Clinical evaluation and periodic laboratory determinations are necessary to monitor changes in fluid balance, electrolyte concentrations, and acid base balance during prolonged parenteral therapy or whenever the condition of the patient warrants such evaluation.

VETERINARY VEDALYTE 7.4 Injection,USP must be used with caution. Excess administration may result in metabolic alkalosis.

Caution must be exercised in the administration of VETERINARY VEDALYTE 7.4 Injection, USP to patients receiving corticosteroids or corticotrophin.

Do not administer unless solution is clear and seal is intact.

Dosage and Administration

As directed by a veterinarian. Dosage is dependent upon the age, weight and clinical condition of the patient, as well as laboratory determinations.

Parenteral drug products should be inspected visually for particulate matter and discoloration prior to administration whenever solution and container permit.

All injections in plastic containers are intended for intravenous administration using sterile equipment.

Additives may be incompatible. Complete information is not available. Those additives known to be incompatible should not be used. Consult with pharmacist, if available. If, in the informed judgment of the veterinarian, it is deemed advisable to introduce additives, use aseptic technique.

Mix thoroughly when additives have been introduced. Do not store solutions containing additives.

OverDosage

In an event of over hydration or solute overload, re-evaluate the patient and institute appropriate corrective measures. See Warnings. Precautions and Adverse Events.

How Supplied

Veterinary VEDALYTE 7.4 Injection, USP in plastic container is available as follows:

Plastic Container:

*PVC Free, DEHP Free, Latex Free Bag.

** The plastic container is fabricated from a specially formulated polyvinyl chloride. The amount of water that can permeate from inside the container into the overwrap is insufficient to affect the solution significantly. Solutions in contact with the plastic container can leach out certain of its chemical components in very small amounts within the expiration period, e.g., di-2-ethylhexyl phthalate (DEHP), upto 5 parts per million. However safety of the plastic has been confirmed in animals according to USP biological tests for plastic containers, as well as tissue culture toxicity studies.

Storage

Exposure of pharmaceutical products to heat should be minimized. Avoid excessive heat. It is recommended the product be stored in the moisture overwrap at room temperature (25ºC/77ºF); brief exposure up to (40ºC/104ºF) does not adversely affect the product.

Direction for use of plastic section

To Open
Tear overwrap down side at slit and remove solution container. Some opacity of the plastic due to moisture absorption during the sterilization process may be observed. This is normal and does not affect the solution quality or safety. The opacity will diminish gradually. Check for minute leaks by squeezing inner bag firmly. If leaks are found, discard solution as sterility may be impaired. If supplemental medication is desired, follow directions below.

Preparation for Administration
1. Suspend container from eyelet support.

2. Remove protector from outlet port at bottom of container.

3. Attach administration set. Refer to complete directions accompanying set.

To Add Medication
WARNING: Additives may be incompatible.

To add medication before solution administration
1. Prepare medication site.

2. Using syringe with 19 to 22 gauge needle, puncture resealable medication port and inject.

3. Mix solution and medication thoroughly. For high density medication such as potassium chloride, squeeze ports while ports are upright and mix thoroughly.

To add medication during solution administration
1. Close clamp on the administration set to stop flow to the patient.

2. Prepare medication site.

3. Using syringe with 19 to 22 gauge needle, puncture resealable medication port and inject.

4. Remove container from IV pole and/or turn to an upright position.

5. Evacuate both ports by squeezing them while container is in the upright position.

6. Mix solution and medication thoroughly.

7. Return container to in-use position and continue administration.

CAUTION: Federal law (USA) restricts this drug to use by or on the order of a licensed veterinarian.

Manufactured for

Vedco, Inc.
5503 Corporate Dr.

St. Joseph, MO 64507 USA

Printed in El Salvador

For a copy of the Safety Data Sheet (SDS) or to report adverse reactions call Vedco, Inc. customer service at 1(888) 708-3326

VEDALYTE is a trademark of Vedco INc., all rights reserved.

© 2016 Vedco, Inc.

Principal Display Panel

NDC 50989-892-16

BIOGALENIC VEDCO

VETERINARY VEDALYTE 7.4 INJECTION, USP

NDC 50989-892-17

BIOGALENIC VEDCO

VETERINARY VEDALYTE 7.4 INJECTION, USP